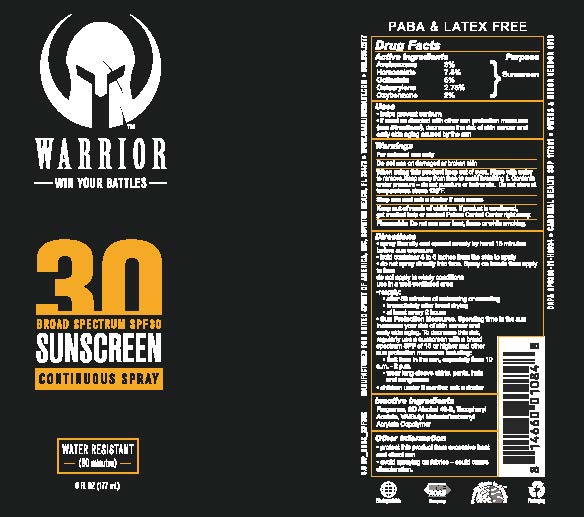 DRUG LABEL: United Spirit of America (Warrior)
NDC: 13630-0237 | Form: SPRAY
Manufacturer: Prime Packaging, Inc.
Category: otc | Type: HUMAN OTC DRUG LABEL
Date: 20220524

ACTIVE INGREDIENTS: AVOBENZONE 24.9 mg/1 mL; HOMOSALATE 62.25 mg/1 mL; OCTISALATE 41.5 mg/1 mL; OCTOCRYLENE 22.825 mg/1 mL; OXYBENZONE 16.6 mg/1 mL
INACTIVE INGREDIENTS: ISOBORNYL ACETATE; DIBUTYL MALEATE; .ALPHA.-TOCOPHEROL ACETATE; ALCOHOL; VINYL ACETATE

Warrior Broad Spectrum SPF 30 Continuous Spray Sunscreen

Active Ingredients

Avobenzone 3 %

Homosalate 7.5%

Octisalate 5 %

Octocrylene 2.75 %

Oxybenzone 2 %

Purpose

Sunscreen

Uses

- helps prevent sunburn
- If used as directed with other sun protection measures (see Directions), decreases the risk of skin cancer and early skin agining caused by the sun

Warnings

For external use only

Do not use on damaged or broken skin.

When using this product keep out of eyes. Rinse with water to remove.

- keep away from face to avoid breathing it.
- Contents under pressure - do not puncture or incinerate. Do not store at temperatures above 120^0F

Stop use and ask a doctor if rash occurs.

Keep out of reach of children. If product is swallowed, get medical help or contact a Poison Control Center right away.

OTHER SAFETY INFORMATION

Flammable: Do not use near heat, flame or while smoking.

Directions

- spray liberally and spread evenly by hand 15 minutes before sun exposure
- hold container 4 to 6 inches from the skin to apply
- do no spray directly into face. Spray on hands then apply to face
- do not apply in windy conditions
- use in well-ventilated area
- reapply:
  - after 80 minutes of swimming or sweating
  - immediately after towel drying
  - at least every 2 hours
- Sun Protection Measures. Spending time in the sun increases your risk of skin cancer and early skin aging. To decrease this risk, regularly use a sunscreen with a broad spectrum SPF of 15 or higher and other sun protection measures including:
  - limit time in the sun, especially from 10 a.m. – 2 p.m.
  - wear long-sleeve shirts, pants, hats, and sunglasses
- children under 6 months: Ask a doctor

Inactive ingredients

Fragrance, SD Alcohol 40-B, Tocopheryl Acetate, VA/Butyl Maleate/Isobornyl Acrylate Copolymer

Other information

- protect this product from excesive heat and direct sun
- avoid spraying on fabrics - could cause discoloration